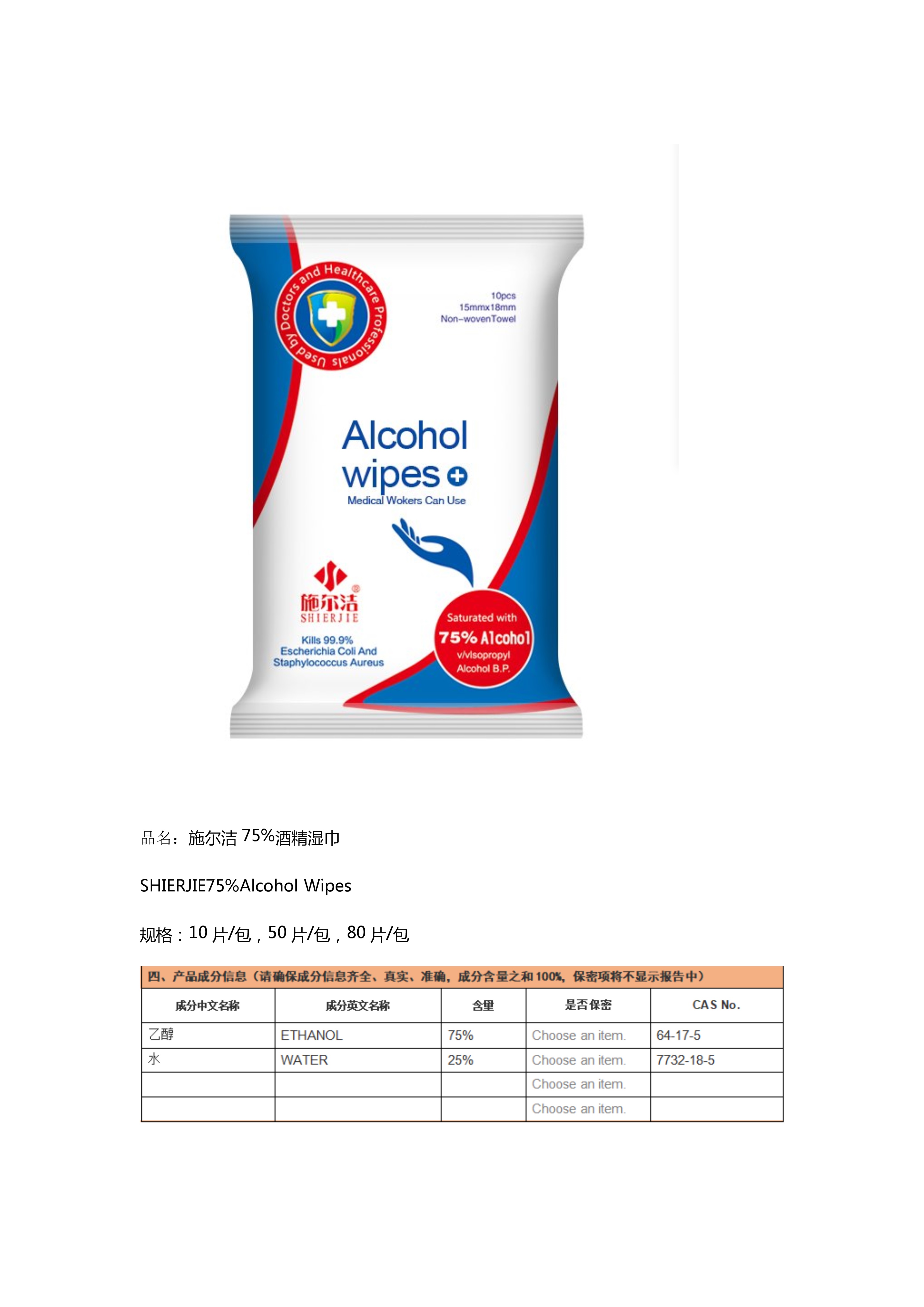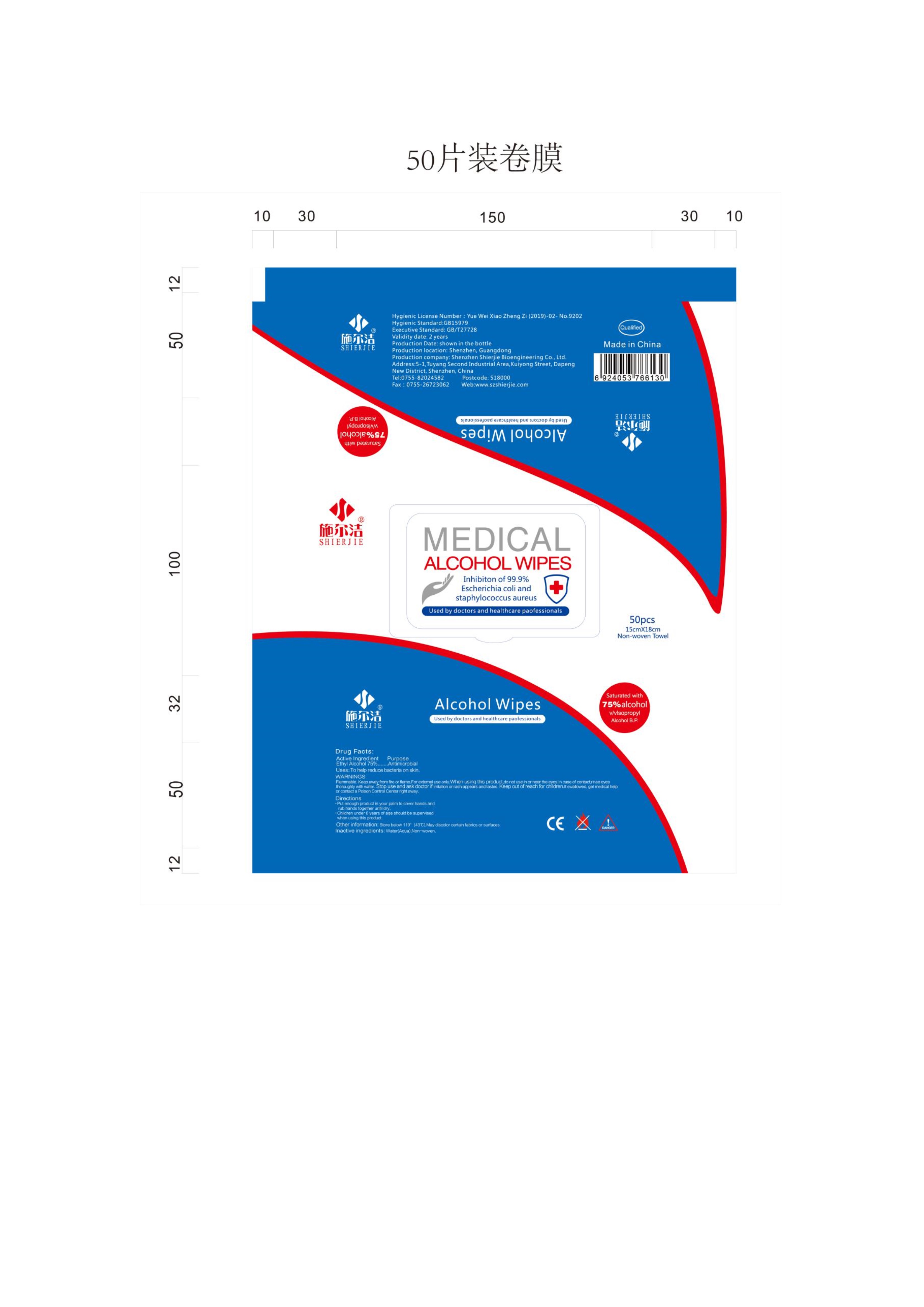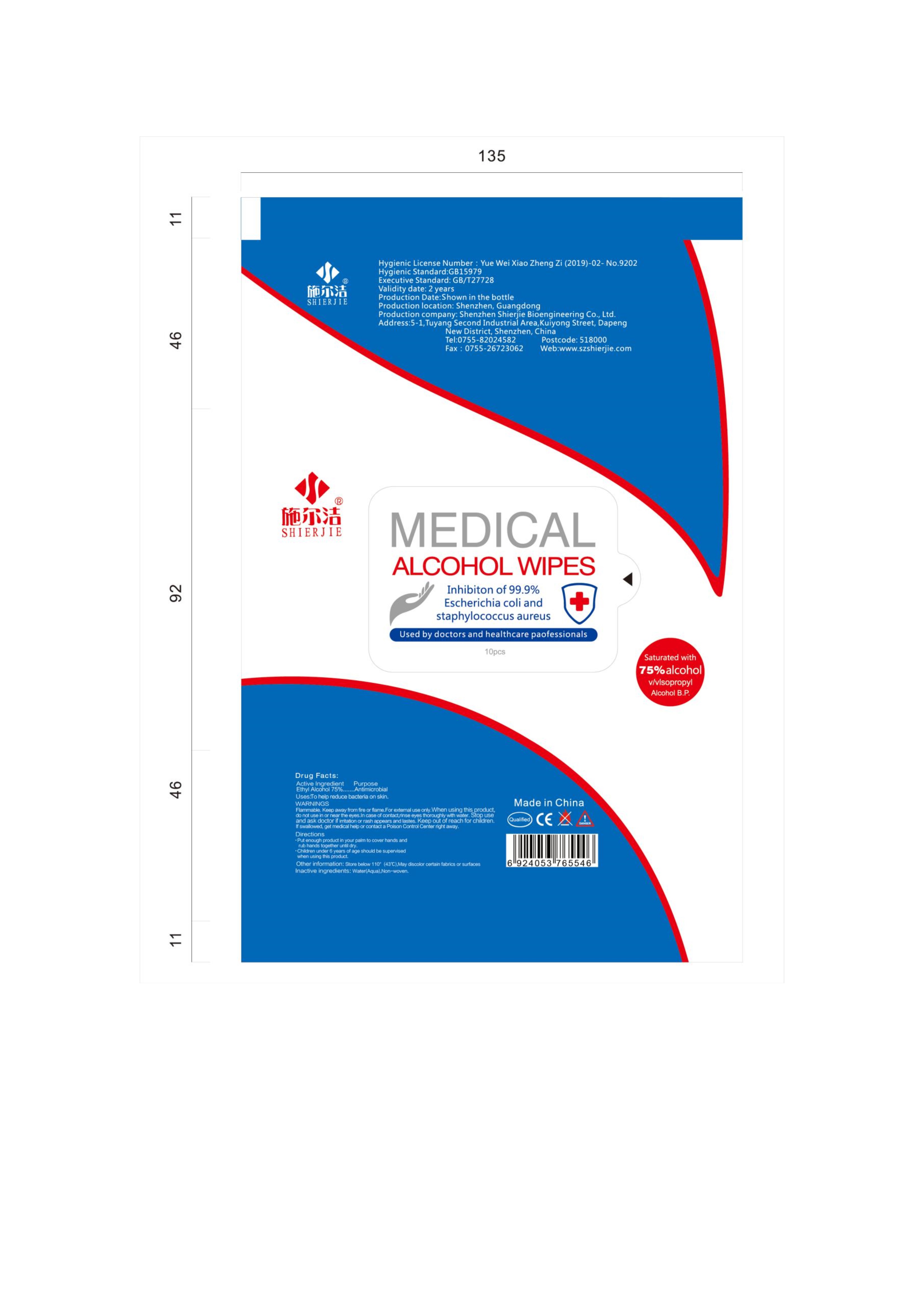 DRUG LABEL: SHIERJIE 75% Alcohol Wipes
NDC: 43116-003 | Form: CLOTH
Manufacturer: Shenzhen Shierjie Biological Engineering Co., LTD
Category: otc | Type: HUMAN OTC DRUG LABEL
Date: 20201122

ACTIVE INGREDIENTS: ALCOHOL 75 mL/100 mL
INACTIVE INGREDIENTS: WATER

43116-003
SHIERJIE 75% Alcohol Wipes

Active Ingredient

Ethyl Alcohol 75%

Purpose

Antimicrobial

Uses

To help reduce bacteria on skin.

Warnings

Flammable. Keep away from fire or flame, For external use only.When using this product,do not use in or near the eyes.In case of contact,rinse eyes thoroughly with water.Stop use and ask doctor if irritation or rash appears and lasts,Keep out of reach for children if swallowed,get medical help of contact a Poison Control Center right away.

Directions

Put enough product in your palm to cover hands and rub hands together until dry.

Children under 6 years of age should be supervised when using this product.

Other information

Store below 110°(43°C)

May discolor certain fabrics or surfaces

Inactive ingredients

Water(Aqua),Non-woven